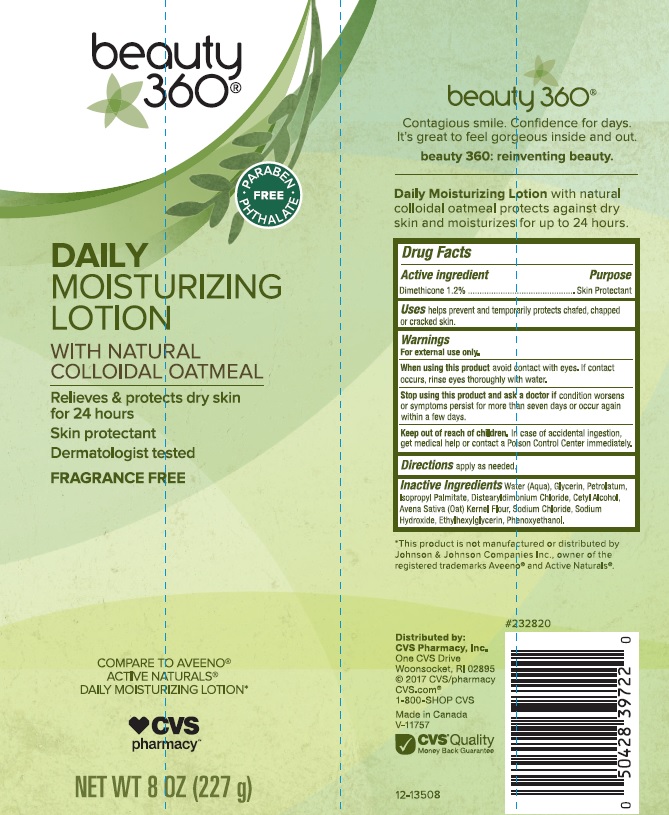 DRUG LABEL: Beauty 360 Daily Moisturizing
NDC: 59779-749 | Form: LOTION
Manufacturer: CVS Pharmacy
Category: otc | Type: HUMAN OTC DRUG LABEL
Date: 20180109

ACTIVE INGREDIENTS: DIMETHICONE 12 mg/1 mL
INACTIVE INGREDIENTS: WATER; GLYCERIN; PETROLATUM; ISOPROPYL PALMITATE; DISTEARYLDIMONIUM CHLORIDE; CETYL ALCOHOL; OATMEAL; SODIUM CHLORIDE; SODIUM HYDROXIDE; ETHYLHEXYLGLYCERIN; PHENOXYETHANOL

Drug Facts

Active ingredient

Dimethicone 1.2%

Purpose

Skin protectant

Uses

Helps prevent and temporarily protects chafed, chapped or cracked skin.

Warnings

For external use only.

When using this product

avoid contact with eyes. If contact occurs, rinse eyes thoroughly with water.

Stop using this product and ask a doctor if

condition worsens or symptoms persist for more than seven days or occur again within a few days.

Keep out of reach of children.

In case of accidental ingestion, get medical help or contact a Poison Control Center immediately.

Directions

apply as needed

Inactive ingredients

Water (Aqua), Glycerin, Petrolatum, Isopropyl Palmitate, Distearyldimonium Chloride, Cetyl Alcohol, Avena Sativa (Oat) Kernel Flour, Sodium Chloride, Sodium Hydroxide, Ethylhexylglycerin, Phenoxyethanol.